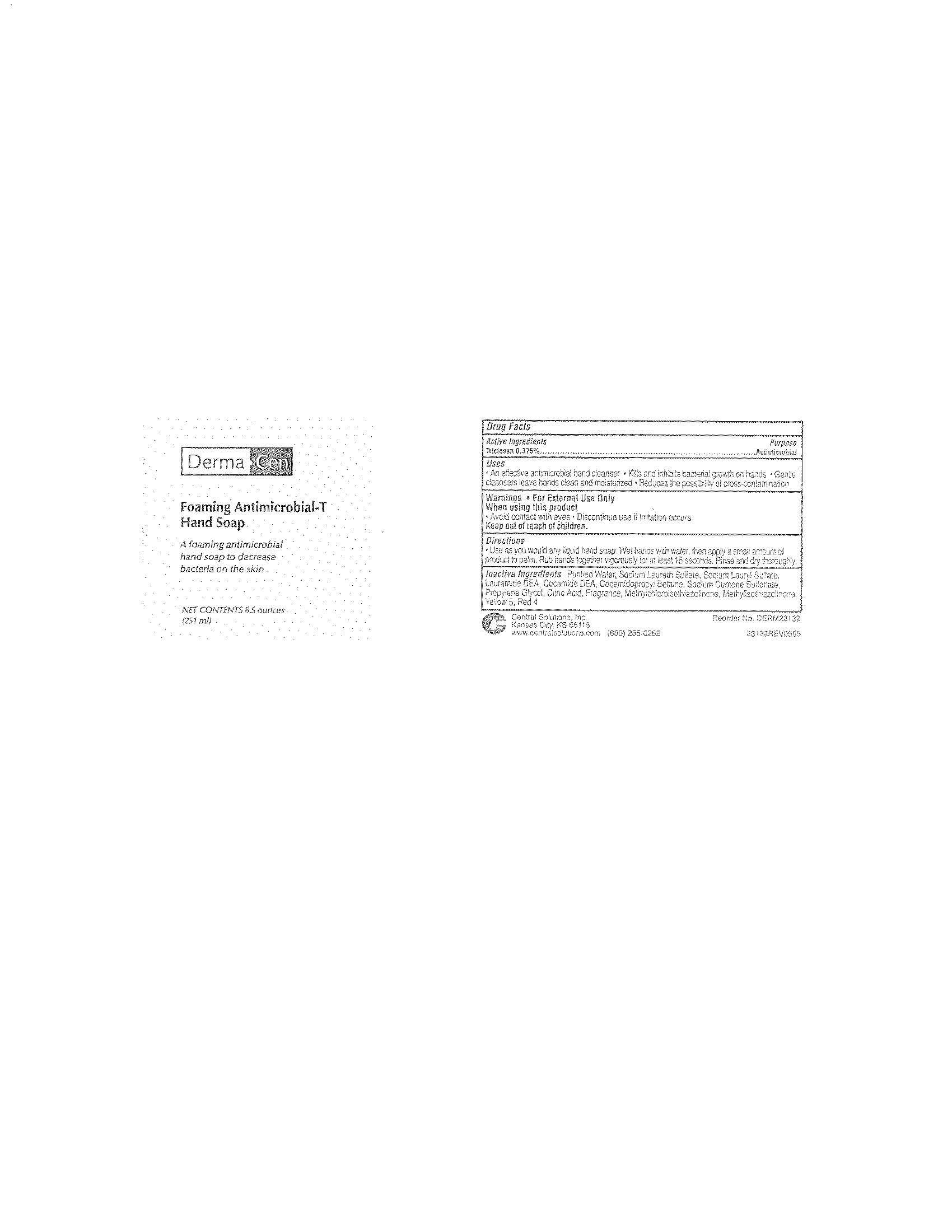 DRUG LABEL: DermaCen Foaming Antimicrobial-T Hand
NDC: 62654-239 | Form: LIQUID
Manufacturer: Central Solutions Inc
Category: otc | Type: HUMAN OTC DRUG LABEL
Date: 20110713

ACTIVE INGREDIENTS: TRICLOSAN 0.375 mL/100 mL
INACTIVE INGREDIENTS: WATER; SODIUM LAURETH SULFATE; SODIUM LAURYL SULFATE; LAURIC DIETHANOLAMIDE; COCO DIETHANOLAMIDE; COCAMIDOPROPYL BETAINE; SODIUM CUMENESULFONATE; PROPYLENE GLYCOL; CITRIC ACID MONOHYDRATE; METHYLCHLOROISOTHIAZOLINONE; METHYLISOTHIAZOLINONE; FD&C YELLOW NO. 5; FD&C RED NO. 4

Drug Facts

Active ingredients

Triclosan 0.375%

Purpose

Antimicrobial

Uses

An effective antimicrobial hand cleanser

Kills and inhibits bacterial growth on hands

Gentle cleansers leave hands clean and moisturized

Reduces the possibility of cross-contamination

Warnings

For External Use Only

When using this product

Avoid contact with eyes

Discontinue use if irritation occurs

Keep out of reach of children.

Directions

Use as you would any liquid hand soap.

Wet hands with water, then apply a small amount of product to palm.

Rub hands together vigorously for at least 15 seconds.

Rinse and dry thoroughly.

Inactive ingredients

Purified Water, Sodium Laureth Sulfate, Sodium Lauryl Sulfate, Lauramide DEA, Cocamide DEA, Cocamidopropyl Betaine, Sodium Cumene Sulfonate, Propylene Glycol, Citric Acid, Fragrance, Methylchloroisothiazolinone, Methylisothiazolinone, Yellow 5, Red 4

PACKAGE LABEL

DermaCen

Foaming Antimicrobial-T

Hand Soap

A foaming antimicrobial

hand soap to decrease bacteria on the skin

Net Contents 8.5 ounces

(251 ml)